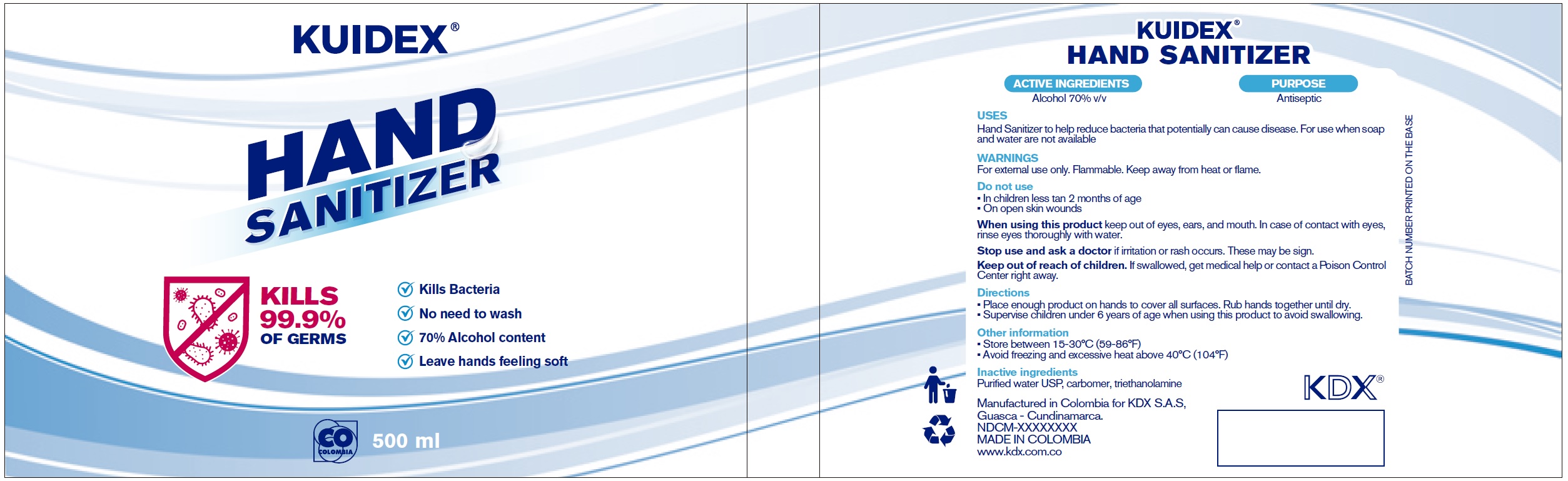 DRUG LABEL: Hand Sanitizer
NDC: 78647-000 | Form: GEL
Manufacturer: KDX S A S
Category: otc | Type: HUMAN OTC DRUG LABEL
Date: 20200729

ACTIVE INGREDIENTS: ALCOHOL 0.7 mL/1 mL
INACTIVE INGREDIENTS: WATER; CARBOMER HOMOPOLYMER, UNSPECIFIED TYPE; TROLAMINE

Hand Sanitizer

ACTIVE INGREDIENTS

Alcohol 70% v/v

PURPOSE

Antiseptic

USES

Hand Sanitizer to help reduce bacteria that potentially can cause disease. For use when soap and water are not available

WARNINGS

For external use only. Flammable. Keep away from heat or flame.

Do not use

• In children less tan 2 months of age
• On open skin wounds

When using this product

keep out of eyes, ears, and mouth. In case of contact with eyes, rinse eyes thoroughly with water.

Stop use and ask a doctor

if irritation or rash occurs. These may be sign.

Keep out of reach of children.

If swallowed, get medical help or contact a Poison Control Center right away.

Directions

• Place enough product on hands to cover all surfaces. Rub hands together until dry.
• Supervise children under 6 years of age when using this product to avoid swallowing.

Other information

• Store between 15-30°C (59-86°F)
• Avoid freezing and excessive heat above 40°C (104°F)

Inactive ingredients

Purified water USP, carbomer, triethanolamine